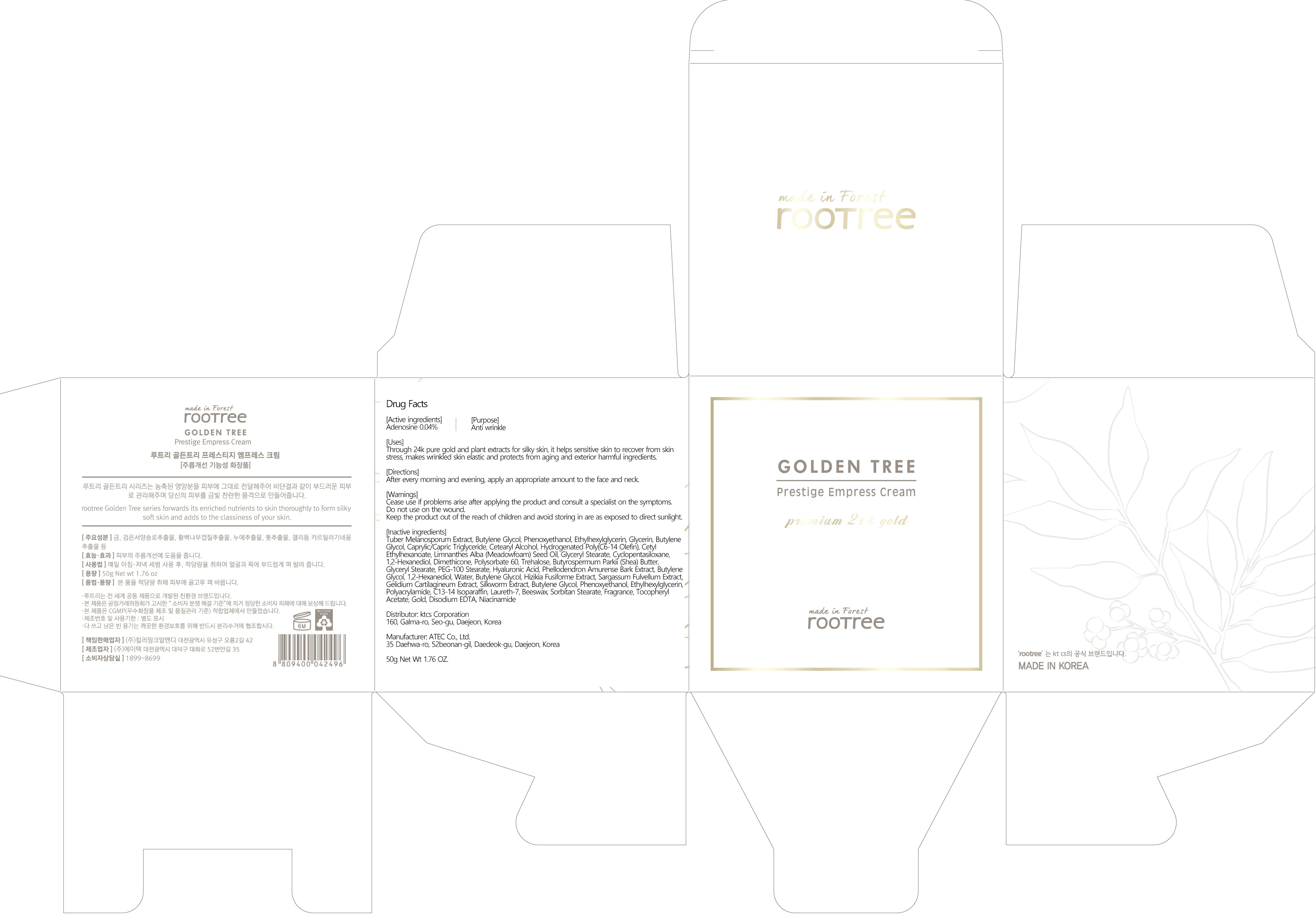 DRUG LABEL: rootree Golden Tree Prestige Empress
NDC: 72441-100 | Form: CREAM
Manufacturer: KTCS Corporation
Category: otc | Type: HUMAN OTC DRUG LABEL
Date: 20191230

ACTIVE INGREDIENTS: Adenosine 0.02 g/50 g
INACTIVE INGREDIENTS: Butylene Glycol; Glycerin

ACTIVE INGREDIENT

Active ingredients: Adenosine 0.04%

INACTIVE INGREDIENT

Inactive ingredients:

Tuber Melanosporum Extract, Butylene Glycol, Phenoxyethanol, Ethylhexylglycerin, Glycerin, Butylene Glycol, Caprylic/Capric Triglyceride, Cetearyl Alcohol, Hydrogenated Poly(C6-14 Olefin), Cetyl Ethylhexanoate, Limnanthes Alba (Meadowfoam) Seed Oil, Glyceryl Stearate, Cyclopentasiloxane, 1,2-Hexanediol, Dimethicone, Polysorbate 60, Trehalose, Butyrospermum Parkii (Shea) Butter, Glyceryl Stearate, PEG-100 Stearate, Hyaluronic Acid, Phellodendron Amurense Bark Extract, Butylene Glycol, 1,2-Hexanediol, Water, Butylene Glycol, Hizikia Fusiforme Extract, Sargassum Fulvellum Extract, Gelidium Cartilagineum Extract, Silkworm Extract, Butylene Glycol, Phenoxyethanol, Ethylhexylglycerin, Polyacrylamide, C13-14 Isoparaffin, Laureth-7, Beeswax, Sorbitan Stearate, Fragrance, Tocopheryl Acetate, Gold, Disodium EDTA, Niacinamide

PURPOSE

Purpose: Anti-wrinkle

WARNINGS

Cease use if problems arise after applying the product and consult a specialist on the symptoms.
Do not use on the wound.
Keep the product out of the reach of children and avoid storing in are as exposed to direct sunlight.

KEEP OUT OF REACH OF CHILDREN

Keep the product out of the reach of children

Uses

Through 24k pure gold and plant extracts for silky skin, it helps sensitive skin to recover from skin stress, makes wrinkled skin elastic and protects from aging and exterior harmful ingredients.

Directions

After every morning and evening, apply an appropriate amount to the face and neck.